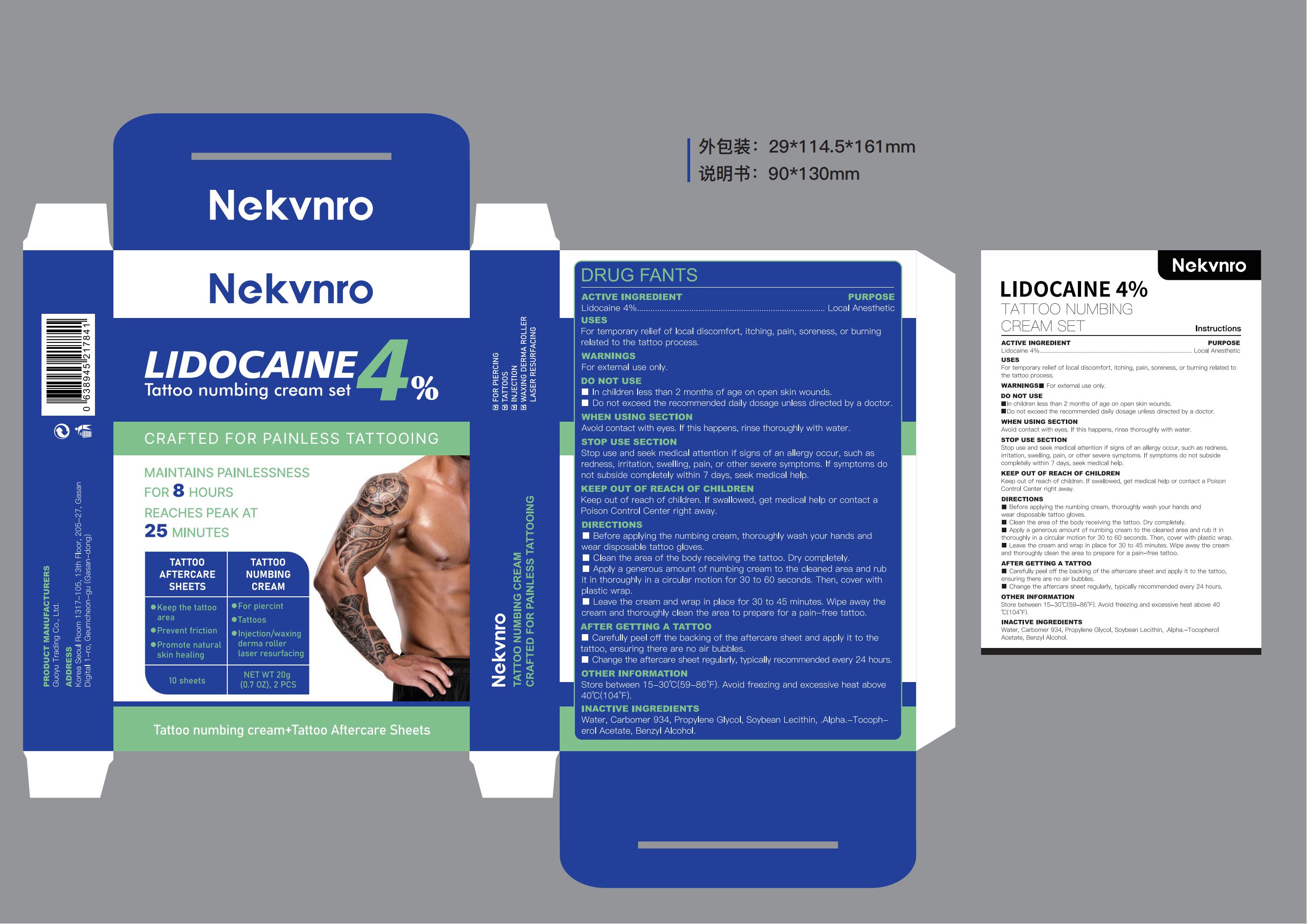 DRUG LABEL: Nekvnro LIDOCAINE 4% Tattoo numbing cream set
NDC: 84844-018 | Form: CREAM
Manufacturer: Guoyu Trading Co., Ltd.
Category: otc | Type: HUMAN OTC DRUG LABEL
Date: 20250220

ACTIVE INGREDIENTS: LIDOCAINE 4 g/100 g
INACTIVE INGREDIENTS: CARBOMER 934; ALPHA-TOCOPHEROL ACETATE; SOYBEAN LECITHIN; BENZYL ALCOHOL; PROPYLENE GLYCOL; WATER

84844-018

Active Ingredient

Lidocaine 4%

Purpose

Local Anesthetic

Use

For temporary relief of local discomfort, itching, pain, soreness, or burning related to the tattoo process.

Warnings

For external use only.

Do not use

■In children less than 2 months of age on open skin wounds.
■Do not exceed the recommended daily dosage unless directed by a doctor.

When Using

section
Avoid contact with eyes. If this happens, rinse thoroughly with water.

Stop Use

section
Stop use and seek medical attention if signs of an allergy occur, such as redness, irritation, swelling, pain, or other severe symptoms. If symptoms do not subside completely within 7 days, seek medical help.

Ask Doctor

Stop use and seek medical attention if signs of an allergy occur, such as redness, irritation, swelling, pain, or other severe symptoms.

■If symptoms persist for more than 7 days or subside but occur again within 3 days, stop use and consult a physician. If symptoms do not subside completely within 7 days, seek medical help.

Keep Oot Of Reach Of Children

Keep out of reach of children. If swallowed, get medical help or contact a Poison Control Center right away.

Directions

■Before applying the numbing cream, thoroughly wash your hands and
wear disposable tattoo gloves.
■Clean the area of the body receiving the tattoo. Dry completely.
■Apply a generous amount of numbing cream to the cleaned area and rub it in thoroughly in a circular motion for 30 to 60 seconds. Then, cover with plastic wrap.
■Leave the cream and wrap in place for 30 to 45 minutes. Wipe away the cream and thoroughly clean the area to prepare for a pain-free tattoo.
After getting a tattoo
Carefully peel off the backing of the aftercare sheet and apply it to the tattoo, ensuring there are no air bubbles.
Change the aftercare sheet regularly, typically recommended every 24 hours.

Other information

Store between 15-30℃(59-86°F). Avoid freezing and excessive heat above 40℃(104°F).

Inactive ingredients

Water ,Carbomer 934 ,Propylene Glycol,Soybean Lecithin,.Alpha.-Tocopherol Acetate,Benzyl Alcohol.